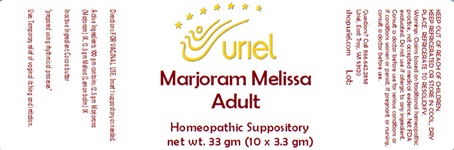 DRUG LABEL: Marjoram Melissa Adult Size
NDC: 48951-7197 | Form: SUPPOSITORY
Manufacturer: Uriel Pharmacy Inc.
Category: homeopathic | Type: HUMAN OTC DRUG LABEL
Date: 20240221

ACTIVE INGREDIENTS: SWEET MARJORAM 1 [hp_X]/1 g; MELISSA OFFICINALIS 1 [hp_X]/1 g
INACTIVE INGREDIENTS: COCOA BUTTER

Marjoram Melissa Adult Size

INDICATIONS AND USAGE

Directions: FOR VAGINAL USE.

DOSAGE AND ADMINISTRATION

Insert 1 suppository as needed.

ACTIVE INGREDIENT

Active Ingredients: 100 gm contains: 12.5 gm Marjorana (Marjoram) 1X, 12.5 gm Melissa (Lemon balm) 1X

Inactive Ingredient: Cocoa butter

"prepared using rhythmical processes"

PURPOSE

Uses: Temporary relief of vaginal itching and irritation.

KEEP OUT OF REACH OF CHILDREN.

WARNINGS

KEEP REFRIGERATED OR STORE IN COOL, DRY PLACE. REFRIGERATE TO RESOLIDIFY.
Warnings: Claims based on traditional homeopathic practice, not accepted medical evidence.
Not FDA evaluated. Do not use if allergic to any ingredient. Consult a doctor before use for
serious conditions or if conditions worsen or persist. If pregnant or nursing, consult a doctor
before use. Do not use if safety seals on box are broken or missing.

Questions? Call 866.642.2858
Uriel, East Troy, WI 53120
shopuriel.com Lot: